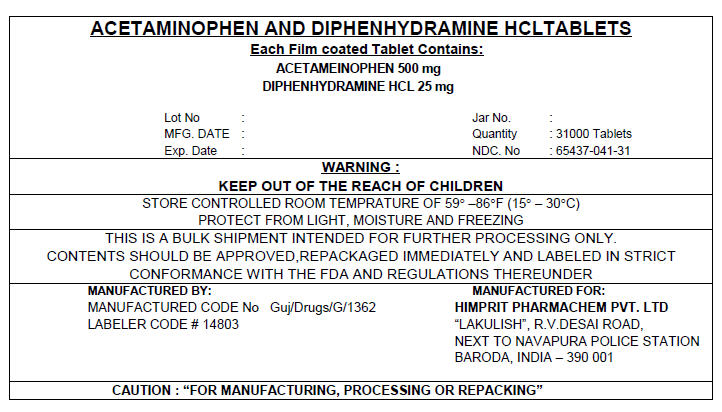 DRUG LABEL: ACETAMINOPHEN AND DIPHENHYDRAMINE HYDROCHLORIDE
NDC: 65437-041 | Form: TABLET, FILM COATED
Manufacturer: HIMPRIT PHARMACHEM PVT LTD
Category: otc | Type: HUMAN OTC DRUG LABEL
Date: 20100615

ACTIVE INGREDIENTS: ACETAMINOPHEN 500 mg/1 1; DIPHENHYDRAMINE HYDROCHLORIDE 25 mg/1 1
INACTIVE INGREDIENTS: SODIUM METABISULFITE; CELLULOSE, MICROCRYSTALLINE; CROSCARMELLOSE SODIUM; STEARIC ACID; POLYETHYLENE GLYCOL; FD&C BLUE NO. 1; TITANIUM DIOXIDE; WATER; SILICON DIOXIDE; FD&C BLUE NO. 2; HYPROMELLOSE; TALC

ACETAINOPHEN AND DIPHENHYDRAMINE HCL TABLETS 500/25 mg

Drug Facts

ACTIVE INGREDIENT

Active ingredients (in each Caplet) | Purpose
Acetaminophen 500 mg | Pain reliever/ fever reducer
Diphenhydramine HCL 25 mg | Sleep Aid

Uses

Temporary relief of occasional headaches and minor aches and pain with accompanying sleeplessness

Warnings

Alcohol Warnings

If you consume 3 or more alcoholic drinks every day, ask your doctor if you should take acetaminophen or other pain relievers/fever reducers. Acetaminophen may cause liver damage.

Do not use

- with any other product containing acetaminophen
- with any other product containing diphenhydramine, even one used on skin
- in children under 12 years of age

Ask a doctor before use if you have

- a breathing problem such as emphysema or chronic bronchitis
- glaucoma
- difficulty in urination due to enlargement of the prostate gland

ASK a doctor or pharmacists before use if you are taking sedatives or tranquilizers

When using this product

- do not exceed recommended dosage
- avoid alcoholic beverages
- marked drowsiness may occur
- do not drive a motor vehicle or operate machinery

Stop use and ask a doctor if

- sleeplessness persists continuously for more than two weeks. Insomnia may be a symptom of a serious underlying medical illness
- new symptoms occur
- redness or swelling is present
- pain gets worse or lasts more than 10 days
- fever gets worse or lasts more than 3 days

PREGNANCY OR BREAST FEEDING

If pregnant or breast-feeding, ask a health professional before use

Keep out of reach of children. In case of accidental overdose get medical help or contact a Poison Control Center right away. Prompt medical attention is critical for adults as well as for children even if you do not notice any signs or symptoms.

Direction

- use as directed
- adults and children 12 years and over : take 2 caplets at bedtime or as directed by a doctor
- Children under 12 years : do not use this adult product in children under 12 years of age; this will provide more than the recommended dose (overdose) and could cause serious health problems.

Other information

- Store at room temperature

Inactive ingredients

croscarmellose sodium, hypromellose, polythlene glycol,sodium metabisulfate, stearic acid,, sodium starch glycolate,collodial silicon dioxide, FD & C blue # 1

PRINCIPAL DISPLAY PANEL 500/25 mg Shipper Label

ACETAMINOPHEN AND DIPHENHYDRAMINE HCL TABLETS
Each Film coated Tablet Contains:
ACETAMEINOPHEN 500 mg
DIPHENHYDRAMINE HCL 25 mg

Lot No :
MFG. DATE :
Exp. Date :
Jar No. :
Quantity : 31000 Tablets
NDC. No : 65437-041-31

WARNING :
KEEP OUT OF THE REACH OF CHILDREN

STORE CONTROLLED ROOM TEMPRATURE OF 59° –86°F (15° – 30°C)
PROTECT FROM LIGHT, MOISTURE AND FREEZING

THIS IS A BULK SHIPMENT INTENDED FOR FURTHER PROCESSING ONLY.
CONTENTS SHOULD BE APPROVED,REPACKAGED IMMEDIATELY AND LABELED IN STRICT
CONFORMANCE WITH THE FDA AND REGULATIONS THEREUNDER

MANUFACTURED BY:
MANUFACTURED CODE No Guj/Drugs/G/1362
LABELER CODE # 14803

MANUFACTURED FOR:
HIMPRIT PHARMACHEM PVT. LTD
"LAKULISH", R.V.DESAI ROAD,
NEXT TO NAVAPURA POLICE STATION
BARODA, INDIA – 390 001

CAUTION : "FOR MANUFACTURING, PROCESSING OR REPACKING"